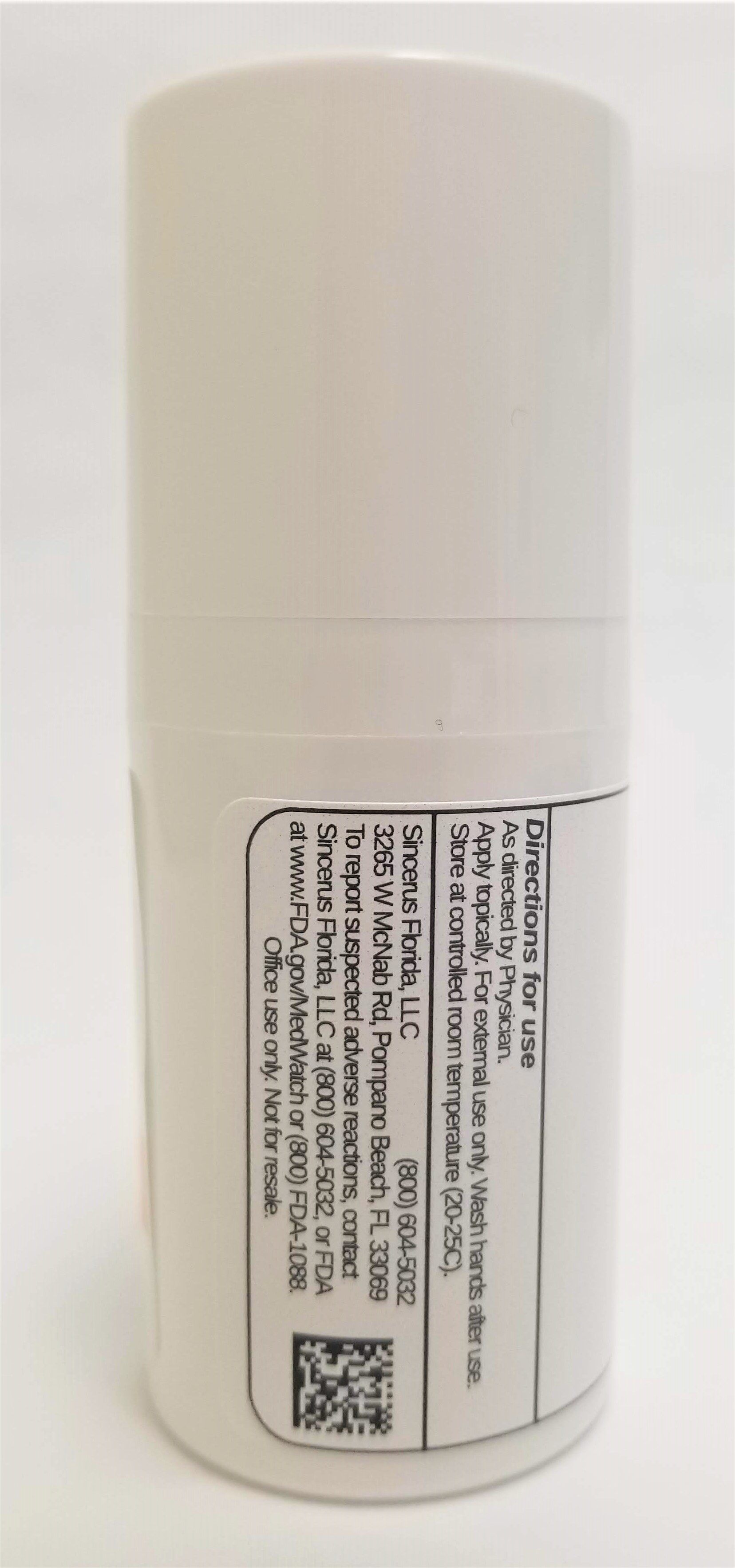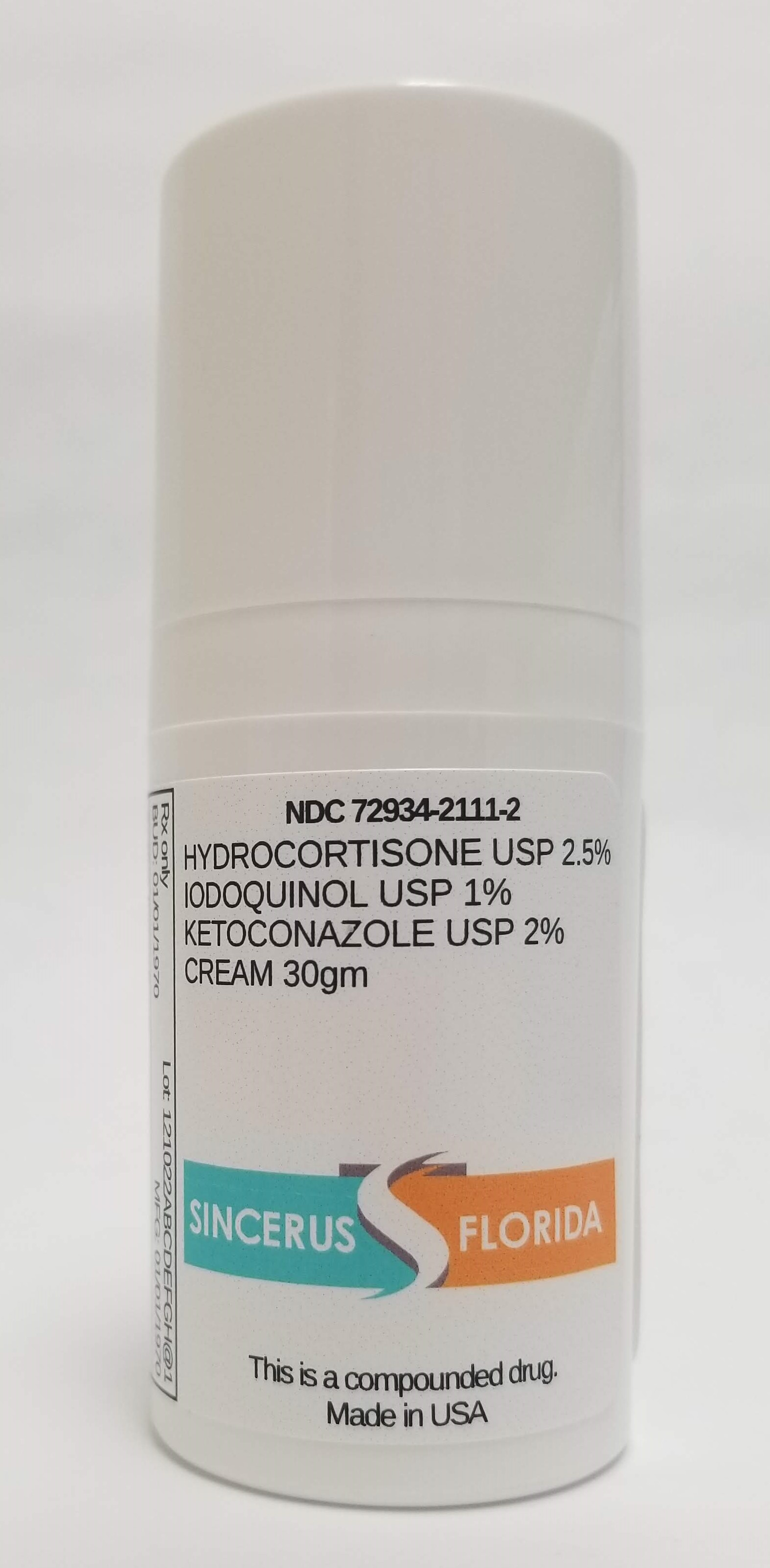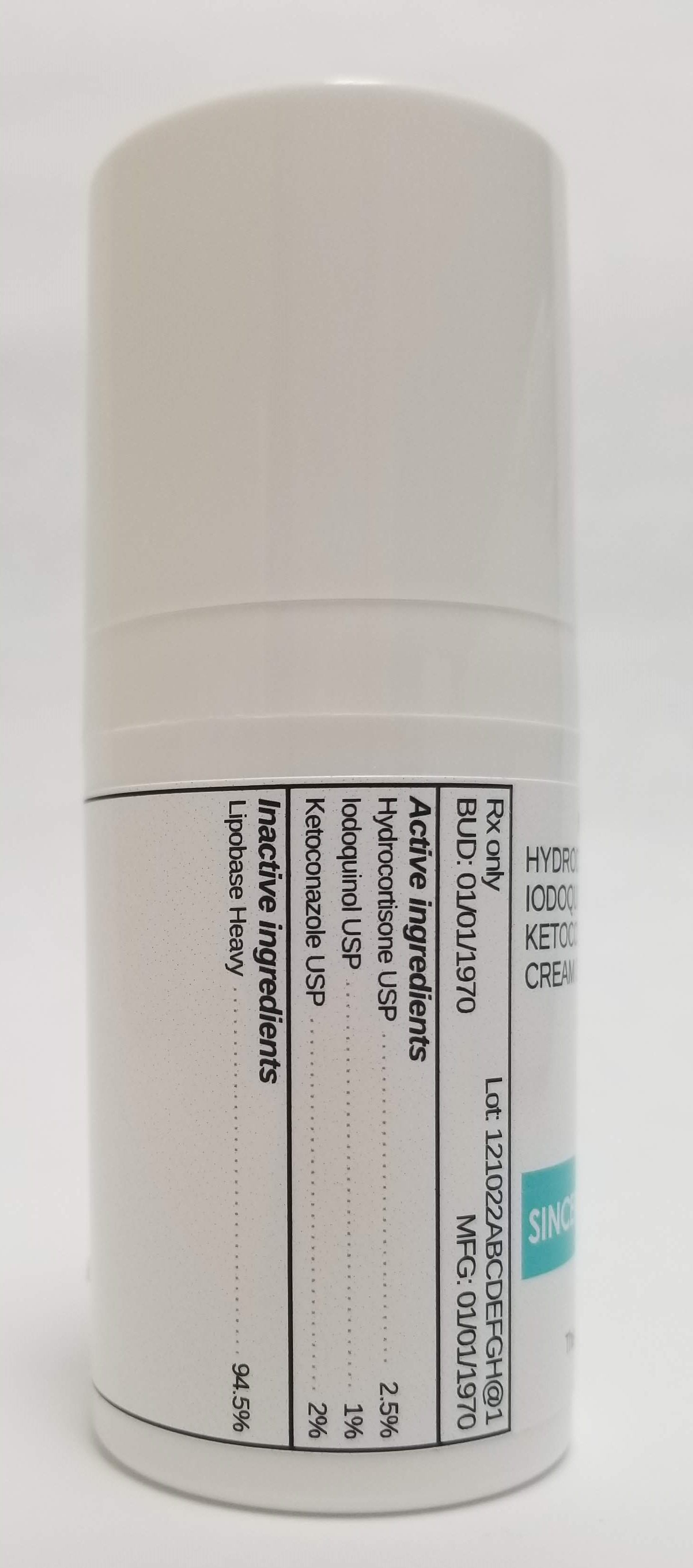 DRUG LABEL: HYDROCORTISONE 2.5% / IODOQUINOL 1% / KETOCONAZOLE 2%
NDC: 72934-2111 | Form: CREAM
Manufacturer: Sincerus Florida, LLC
Category: prescription | Type: HUMAN PRESCRIPTION DRUG LABEL
Date: 20190516

ACTIVE INGREDIENTS: HYDROCORTISONE 2.5 g/100 g; IODOQUINOL 1 g/100 g; KETOCONAZOLE 2 g/100 g

HYDROCORTISONE 2.5% / IODOQUINOL 1% / KETOCONAZOLE 2%